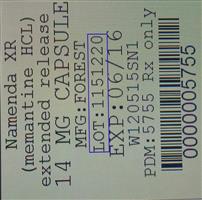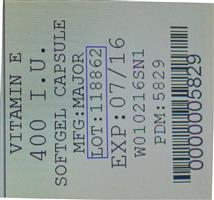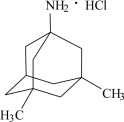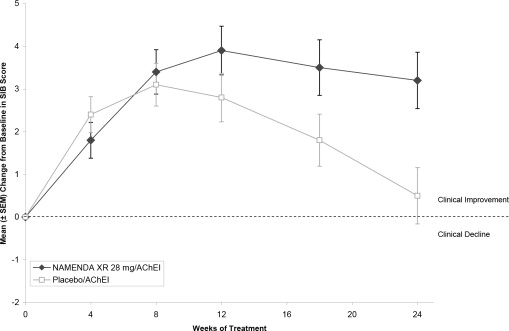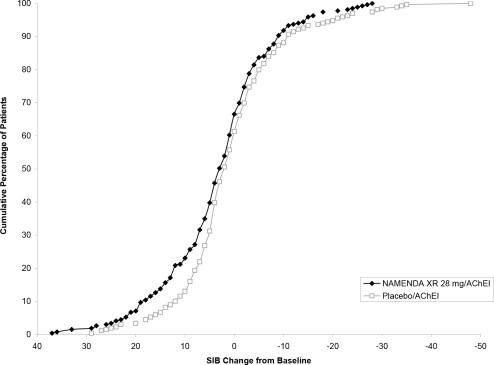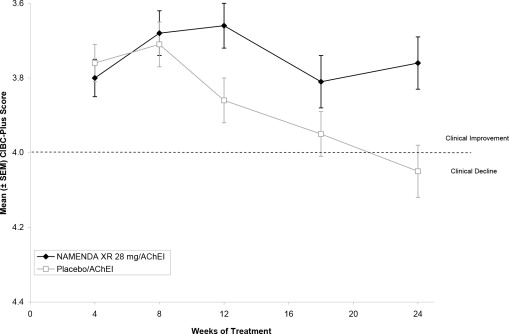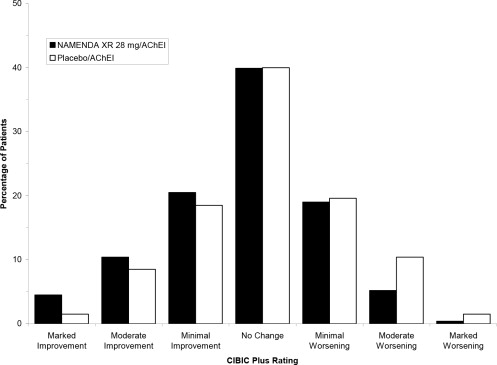 DRUG LABEL: Namenda
                                    
NDC: 68151-5755 | Form: CAPSULE, EXTENDED RELEASE
Manufacturer: Carilion Materials Management
Category: prescription | Type: HUMAN PRESCRIPTION DRUG LABEL
Date: 20171228

ACTIVE INGREDIENTS: MEMANTINE HYDROCHLORIDE 14 mg/1 1
INACTIVE INGREDIENTS: SUCROSE; POVIDONE K30; HYPROMELLOSE 2910 (15 MPA.S); TALC; POLYETHYLENE GLYCOL 400; POLYETHYLENE GLYCOL 8000; ETHYLCELLULOSE (100 MPA.S); AMMONIA

HIGHLIGHTS OF PRESCRIBING INFORMATION

These highlights do not include all the information needed to use NAMENDA XR capsules safely and effectively. See full prescribing information for NAMENDA XR capsules.
NAMENDA XR (memantine hydrochloride) extended release capsules, for oral use
Initial U.S. Approval: 2003

1 INDICATIONS AND USAGE

NAMENDA XR is an NMDA receptor antagonist indicated for the treatment of moderate to severe dementia of the Alzheimer's type (1)

2 DOSAGE AND ADMINISTRATION

- The recommended starting dose of NAMENDA XR is 7 mg once daily; the dose should be increased in 7 mg increments to the recommended maintenance dose of 28 mg once daily; the minimum recommended interval between dose increases is one week (2.1)
- Patients with severe renal impairment: the recommended maintenance dose of NAMENDA XR is 14 mg once daily (2.3)

3 DOSAGE FORMS AND STRENGTHS

NAMENDA XR is available as an extended-release capsule in the following strengths: 7 mg, 14 mg, 21 mg, 28 mg (3)

4 CONTRAINDICATIONS

NAMENDA XR is contraindicated in patients with known hypersensitivity to memantine hydrochloride or to any excipients used in the formulation (4)

5 WARNINGS AND PRECAUTIONS

Conditions that raise urine pH may decrease the urinary elimination of memantine resulting in increased plasma levels of memantine (5.1, 7.1)

6 ADVERSE REACTIONS

The most commonly observed adverse reactions occurring at a frequency of at least 5% and greater than placebo with administration of NAMENDA XR 28 mg/day were headache, diarrhea and dizziness (6.1)

To report SUSPECTED ADVERSE REACTIONS, contact Allergan at 1-800-433-8871 or FDA at 1-800-FDA-1088 or www.fda.gov/medwatch.

FULL PRESCRIBING INFORMATION

1 INDICATIONS AND USAGE

NAMENDA XR (memantine hydrochloride) extended-release capsules are indicated for the treatment of moderate to severe dementia of the Alzheimer's type.

2 DOSAGE AND ADMINISTRATION

2.1 Recommended Dosing

The dosage of NAMENDA XR shown to be effective in a controlled clinical trial is 28 mg once daily.

The recommended starting dose of NAMENDA XR is 7 mg once daily. The dose should be increased in 7 mg increments to the recommended maintenance dose of 28 mg once daily. The minimum recommended interval between dose increases is one week. The dose should only be increased if the previous dose has been well tolerated. The maximum recommended dose is 28 mg once daily.

NAMENDA XR can be taken with or without food. NAMENDA XR capsules can be taken intact or may be opened, sprinkled on applesauce, and thereby swallowed. The entire contents of each NAMENDA XR capsule should be consumed; the dose should not be divided.

Except when opened and sprinkled on applesauce, as described above, NAMENDA XR should be swallowed whole. NAMENDA XR capsules should not be divided, chewed, or crushed.

If a patient misses a single dose of NAMENDA XR, that patient should not double up on the next dose. The next dose should be taken as scheduled. If a patient fails to take NAMENDA XR for several days, dosing may need to be resumed at lower doses and retitrated as described above.

2.2 Switching from NAMENDA to NAMENDA XR Capsules

Patients treated with NAMENDA may be switched to NAMENDA XR capsules as follows:

It is recommended that a patient who is on a regimen of 10 mg twice daily of NAMENDA be switched to NAMENDA XR 28 mg once daily capsules the day following the last dose of 10 mg NAMENDA. There is no study addressing the comparative efficacy of these 2 regimens.

In a patient with severe renal impairment, it is recommended that a patient who is on a regimen of 5 mg twice daily of NAMENDA be switched to NAMENDA XR 14 mg once daily capsules the day following the last dose of 5 mg NAMENDA.

2.3 Dosing in Patients with Renal Impairment

In patients with severe renal impairment (creatinine clearance of 5 – 29 mL/min, based on the Cockcroft-Gault equation), the recommended maintenance dose (and maximum recommended dose) is 14 mg/day [see Clinical Pharmacology (12.3)].

3 DOSAGE FORMS AND STRENGTHS

Each capsule contains 7 mg, 14 mg, 21 mg, or 28 mg of memantine HCl.

- The 7 mg capsules are a yellow opaque capsule, with “FLI 7 mg” black imprint.
- The 14 mg capsules are a yellow cap and dark green opaque body capsule, with “FLI 14 mg” black imprint on the yellow cap.
- The 21 mg capsules are a white to off-white cap and dark green opaque body capsule, with “FLI 21 mg” black imprint on the white to off-white cap.
- The 28 mg capsules are a dark green opaque capsule, with “FLI 28 mg” white imprint.

4 CONTRAINDICATIONS

NAMENDA XR is contraindicated in patients with known hypersensitivity to memantine hydrochloride or to any excipients used in the formulation.

5 WARNINGS AND PRECAUTIONS

5.1 Genitourinary Conditions

Conditions that raise urine pH may decrease the urinary elimination of memantine resulting in increased plasma levels of memantine [see Drug Interactions (7.1)].

6 ADVERSE REACTIONS

6.1 Clinical Trials Experience

NAMENDA XR was evaluated in a double-blind placebo-controlled trial in which a total of 676 patients with moderate to severe dementia of the Alzheimer's type (341 patients on NAMENDA XR 28 mg/day and 335 patients on placebo) were treated for up to 24 weeks.

Because clinical trials are conducted under widely varying conditions, adverse reaction rates observed in the clinical trials of a drug cannot be directly compared to rates in the clinical trials of another drug and may not reflect the rates observed in practice.

Adverse Reactions Leading to Discontinuation

In the placebo-controlled clinical trial of NAMENDA XR, the proportion of patients in the NAMENDA XR group and the placebo group who discontinued treatment due to adverse reactions was 10% and 6%, respectively. The most common adverse reaction that led to treatment discontinuation in the NAMENDA XR group was dizziness, at a rate of 1.5%.

Most Common Adverse Reactions

The most commonly observed adverse reactions seen in patients administered NAMENDA XR in the controlled clinical trial, defined as those occurring at a frequency of at least 5% in the NAMENDA XR group and at a frequency higher than placebo, were headache, diarrhea and dizziness.

Table 1 lists adverse reactions that were observed at an incidence of ≥ 2% in the NAMENDA XR group and occurred at a rate greater than placebo.

Table 1: Adverse reactions observed with a frequency of ≥ 2% in the NAMENDA XR group and at a rate greater than placebo
Adverse reaction | Placebo (n = 335) % | NAMENDA XR 28mg (n = 341) %
Gastrointestinal Disorders
Diarrhea | 4 | 5
Constipation | 1 | 3
Abdominal pain | 1 | 2
Vomiting | 1 | 2
Infections and infestations
Influenza | 3 | 4
Investigations
Weight, increased | 1 | 3
Musculoskeletal and connective tissue disorders
Back pain | 1 | 3
Nervous system disorders
Headache | 5 | 6
Dizziness | 1 | 5
Somnolence | 1 | 3
Psychiatric disorders
Anxiety | 3 | 4
Depression | 1 | 3
Aggression | 1 | 2
Renal and urinary disorders
Urinary incontinence | 1 | 2
Vascular disorders
Hypertension | 2 | 4
Hypotension | 1 | 2

Seizure

Memantine has not been systematically evaluated in patients with a seizure disorder. In clinical trials of memantine, seizures occurred in 0.3% of patients treated with memantine and 0.6% of patients treated with placebo.

6.2 Postmarketing Experience

The following adverse reactions have been identified during post-approval use of memantine.

Because these reactions are reported voluntarily from a population of uncertain size, it is not always possible to reliably estimate their frequency or establish a causal relationship to drug exposure. These reactions include:

Blood and Lymphatic System Disorders: agranulocytosis, leukopenia (including neutropenia), pancytopenia, thrombocytopenia, thrombotic thrombocytopenic purpura.

Cardiac Disorders: cardiac failure congestive.

Gastrointestinal disorders: pancreatitis.

Hepatobiliary Disorders: hepatitis.

Psychiatric Disorders: suicidal ideation.

Renal and Urinary Disorders: acute renal failure (including increased creatinine and renal insufficiency).

Skin Disorders: Stevens Johnson syndrome.

7 DRUG INTERACTIONS

7.1 Drugs That Make the Urine Alkaline

The clearance of memantine was reduced by about 80% under alkaline urine conditions at pH 8. Therefore, alterations of urine pH towards the alkaline condition may lead to an accumulation of the drug with a possible increase in adverse effects. Urine pH is altered by diet, drugs (e.g. carbonic anhydrase inhibitors, sodium bicarbonate) and clinical state of the patient (e.g. renal tubular acidosis or severe infections of the urinary tract). Hence, memantine should be used with caution under these conditions.

7.2 Use with other N-methyl-D-aspartate (NMDA) Antagonists

The combined use of NAMENDA XR with other NMDA antagonists (amantadine, ketamine, and dextromethorphan) has not been systematically evaluated and such use should be approached with caution.

8. USE IN SPECIFIC POPULATIONS

8.1 Pregnancy

Pregnancy Category B

There are no adequate and well-controlled studies of memantine in pregnant women. NAMENDA XR should be used during pregnancy only if the potential benefit justifies the potential risk to the fetus.

Memantine given orally to pregnant rats and pregnant rabbits during the period of organogenesis was not teratogenic up to the highest doses tested (18 mg/kg/day in rats and 30 mg/kg/day in rabbits, which are 6 and 21 times, respectively, the maximum recommended human dose [MRHD] on a mg/m^2 basis).

Slight maternal toxicity, decreased pup weights and an increased incidence of non-ossified cervical vertebrae were seen at an oral dose of 18 mg/kg/day in a study in which rats were given oral memantine beginning pre-mating and continuing through the postpartum period. Slight maternal toxicity and decreased pup weights were also seen at this dose in a study in which rats were treated from day 15 of gestation through the post-partum period. The no-effect dose for these effects was 6 mg/kg, which is 2 times the MRHD on a mg/m^2 basis.

8.3 Nursing Mothers

It is not known whether memantine is excreted in human milk. Because many drugs are excreted in human milk, caution should be exercised when Namenda XR is administered to a nursing mother.

8.4 Pediatric Use

Safety and effectiveness in pediatric patients have not been established.

Memantine failed to demonstrate efficacy in two 12-week controlled clinical studies of 578 pediatric patients aged 6-12 years with autism spectrum disorders (ASD), including autism Asperger's disorder and Pervasive Development Disorder - Not Otherwise Specified (PDD-NOS). Memantine has not been studied in pediatric patients under 6 years of age or over 12 years of age. Memantine treatment was initiated at 3 mg/day and the dose was escalated to the target dose (weight-based) by week 6. Oral doses of memantine 3, 6, 9, or 15 mg extended-release capsules were administered once daily to patients with weights < 20 kg, 20-39 kg, 40-59 kg and ≥ 60 kg, respectively.

In a randomized, 12-week double-blind, placebo-controlled parallel study (Study A) in patients with autism, there was no statistically significant difference in the Social Responsiveness Scale (SRS) total raw score between patients randomized to memantine (n=54) and those randomized to placebo (n=53). In a 12-week responder-enriched randomized withdrawal study (Study B) in 471 patients with ASD, there was no statistically significant difference in the loss of therapeutic response rates between patients randomized to remain on full-dose memantine (n=153) and those randomized to switch to placebo (n=158).

The overall safety profile of memantine in pediatric patients was generally consistent with the known safety profile in adults [see Adverse Reactions (6.1)].

In Study A, the adverse reactions in the memantine group (n=56) that were reported in at least 5% of patients and twice that in the placebo group (N=58) are listed in Table 2:

Table 2: Study A Commonly Reported Adverse Reactions With a Frequency ≥ 5% and Twice That in Placebo
Adverse Reaction | Memantine N=56 | Placebo N=58
Cough | 8.9% | 3.4%
Influenza | 7.1% | 3.4%
Rhinorrhea | 5.4% | 0%
Agitation | 5.4% | 1.7%
Discontinuations due to adverse reactionsa
Aggression | 3.6% | 1.7%
Irritability | 1.8% | 3.4%
a Reported adverse reactions leading to discontinuation in more than one patient in either treatment group.

The adverse reactions that were reported in at least 5% of patients in the 12-48 week open-label study to identify responders to enroll in Study B are listed in Table 3:

Table 3: 12-48 Week Open Label Lead-In study to Study B Commonly Reported Adverse Reactions With a Frequency ≥ 5%
Adverse Reaction | Memantine N=903
Headache | 8.0%
Nasopharyngitis | 6.3%
Pyrexia | 5.8%
Irritability | 5.4%
Discontinuations due to adverse reactionsa
Irritability | 1.2%
Aggression | 1.0%
a At least 1% incidence of adverse reactions leading to premature discontinuation.

In the randomized withdrawal study (Study B), the adverse reaction in patients randomized to placebo (n=160) and reported in at least 5% of patients and twice that of the full-dose memantine treatment group (n=157) was irritability (5.0% vs 2.5%).

In a juvenile animal study, male and female juvenile rats were administered memantine (15, 30, and 45 mg/kg/day) starting on postnatal day (PND) 14 through PND 70. Body weights were reduced at 45 mg/kg/day. Delays in sexual maturation were noted in male and female rats at doses ≥ 30 mg/kg/day. Memantine induced neuronal lesions in several areas of the brain on PND 15 and 17 at doses ≥ 30 mg/kg/day. Behavioral toxicity (decrease percent of auditory startle habituation) was noted for animals in the 45 mg/kg/day dose group. The 15 mg/kg/day dose was considered the No-Observed-Adverse-Effect-Level (NOAEL) for this study.

In a second juvenile rat toxicity study, male and female juvenile rats were administered memantine (1, 3, 8, 15, 30, and 45 mg/kg/day) starting on postnatal day (PND) 7 through PND 70. Due to early memantine-related mortality, the 30 and 45 mg/kg/day dose groups were terminated without further evaluation. Memantine induced apoptosis or neuronal degeneration in several areas of the brain on PND 8, 10, and 17 at a dose of 15 mg/kg/day. The NOAEL for apoptosis and neuronal degeneration was 8 mg/kg/day. Behavioral toxicity (effects on motor activity, auditory startle habituation, and learning and memory) was noted at doses ≥ 3 mg/kg/day during treatment, but was not seen after drug discontinuation. Therefore, the 1 mg/kg/day dose was considered the NOAEL for the neurobehavioral effect in this study.

8.5 Geriatric Use

The majority of people with Alzheimer's disease are 65 years and older. In the clinical study of memantine HCl extended-release, the mean age of patients was approximately 77; over 91% of patients were 65 years and older, 67% were 75 years and older, and 14% were at or above 85 years of age. The efficacy and safety data presented in the clinical trials section were obtained from these patients. There were no clinically meaningful differences in most adverse reactions reported by patient groups ≥ 65 years old and < 65 year old.

8.6 Renal Impairment

No dosage adjustment is needed in patients with mild or moderate renal impairment. A dosage reduction is recommended in patients with severe renal impairment [see Dosage and Administration (2.3) and Clinical Pharmacology (12.3)].

8.7 Hepatic Impairment

No dosage adjustment is needed in patients with mild or moderate hepatic impairment. Namenda XR was not studied in patients with severe hepatic impairment [see Clinical Pharmacology (12.3)].

10 OVERDOSAGE

Signs and symptoms most often accompanying overdosage with other formulations of memantine in clinical trials and from worldwide marketing experience, alone or in combination with other drugs and/or alcohol, include agitation, asthenia, bradycardia, confusion, coma, dizziness, ECG changes, increased blood pressure, lethargy, loss of consciousness, psychosis, restlessness, slowed movement, somnolence, stupor, unsteady gait, visual hallucinations, vertigo, vomiting, and weakness. The largest known ingestion of memantine worldwide was 2 grams in an individual who took memantine in conjunction with unspecified antidiabetic medications. This person experienced coma, diplopia, and agitation, but subsequently recovered.

One patient participating in a NAMENDA XR clinical trial unintentionally took 112 mg of NAMENDA XR daily for 31 days and experienced an elevated serum uric acid, elevated serum alkaline phosphatase, and low platelet count.

Fatal outcome has been very rarely been reported with memantine, and the relationship to memantine was unclear.

Because strategies for the management of overdose are continually evolving, it is advisable to contact a poison control center to determine the latest recommendations for the management of an overdose of any drug. As in any cases of overdose, general supportive measures should be utilized, and treatment should be symptomatic.

Elimination of memantine can be enhanced by acidification of urine.

11 DESCRIPTION

NAMENDA XR is an orally active NMDA receptor antagonist. The chemical name for memantine hydrochloride is 1-amino-3,5-dimethyladamantane hydrochloride with the following structural formula:

The molecular formula is C12H21N•HCl and the molecular weight is 215.76. Memantine

HCl occurs as a fine white to off-white powder and is soluble in water.

NAMENDA XR capsules are supplied for oral administration as 7, 14, 21, and 28 mg capsules. Each capsule contains extended release beads with the labeled amount of memantine HCl and the following inactive ingredients: sugar spheres, polyvinylpyrrolidone, hypromellose, talc, polyethylene glycol, ethylcellulose, ammonium hydroxide, oleic acid, and medium chain triglycerides in hard gelatin capsules.

12 CLINICAL PHARMACOLOGY

12.1 Mechanism of Action

Persistent activation of central nervous system N-methyl-D-aspartate (NMDA) receptors by the excitatory amino acid glutamate has been hypothesized to contribute to the symptomatology of Alzheimer's disease. Memantine is postulated to exert its therapeutic effect through its action as a low to moderate affinity uncompetitive (open-channel) NMDA receptor antagonist which binds preferentially to the NMDA receptor-operated cation channels. There is no evidence that memantine prevents or slows neurodegeneration in patients with Alzheimer's disease.

12.2 Pharmacodynamics

Memantine showed low to negligible affinity for GABA, benzodiazepine, dopamine, adrenergic, histamine and glycine receptors and for voltage-dependent Ca^2+, Na+, or K^+ channels. Memantine also showed antagonistic effects at the 5HT3 receptor with a potency similar to that for the NMDA receptor and blocked nicotinic acetylcholine receptors with one-sixth to one-tenth the potency.

In vitro studies have shown that memantine does not affect the reversible inhibition of acetylcholinesterase by donepezil, galantamine, or tacrine.

12.3 Pharmacokinetics

Memantine is well absorbed after oral administration and has linear pharmacokinetics over the therapeutic dose range. It is excreted predominantly unchanged in urine and has a terminal elimination half-life of about 60-80 hours. In a study comparing 28 mg once daily NAMENDA XR to 10 mg twice daily NAMENDA, the Cmax and AUC0-24 values were 48% and 33% higher for the XR dosage regimen, respectively.

Absorption

After multiple dose administration of NAMENDA XR, memantine peak concentrations occur around 9-12 hours post-dose. There is no difference in the absorption of NAMENDA XR when the capsule is taken intact or when the contents are sprinkled on applesauce.

There is no difference in memantine exposure, based on Cmax or AUC, for NAMENDA XR whether that drug product is administered with food or on an empty stomach. However, peak plasma concentrations are achieved about 18 hours after administration with food versus approximately 25 hours after administration on an empty stomach.

Distribution

The mean volume of distribution of memantine is 9-11 L/kg and the plasma protein binding is low (45%).

Metabolism

Memantine undergoes partial hepatic metabolism. The hepatic microsomal CYP450 enzyme system does not play a significant role in the metabolism of memantine.

Elimination

Memantine is excreted predominantly in the urine, unchanged, and has a terminal elimination half-life of about 60-80 hours. About 48% of administered drug is excreted unchanged in urine; the remainder is converted primarily to three polar metabolites which possess minimal NMDA receptor antagonistic activity: the N-glucuronide conjugate, 6-hydroxy memantine, and 1-nitroso-deaminated memantine. A total of 74% of the administered dose is excreted as the sum of the parent drug and the N-glucuronide conjugate. Renal clearance involves active tubular secretion moderated by pH dependent tubular reabsorption.

Specific Populations

Elderly

The pharmacokinetics of memantine in young and elderly subjects are similar.

Gender

Following multiple dose administration of memantine HCl 20 mg daily, females had about 45% higher exposure than males, but there was no difference in exposure when body weight was taken into account.

Renal Impairment

Memantine pharmacokinetics were evaluated following single oral administration of 20 mg memantine HCl in 8 subjects with mild renal impairment (creatinine clearance, CLcr, > 50 – 80 mL/min), 8 subjects with moderate renal impairment (CLcr 30 – 49 mL/min), 7 subjects with severe renal impairment (CLcr 5 – 29 mL/min) and 8 healthy subjects (CLcr > 80 mL/min) matched as closely as possible by age, weight and gender to the subjects with renal impairment. Mean AUC0-∞ increased by 4%, 60%, and 115% in subjects with mild, moderate, and severe renal impairment, respectively, compared to healthy subjects. The terminal elimination half-life increased by 18%, 41%, and 95% in subjects with mild, moderate, and severe renal impairment, respectively, compared to healthy subjects.

Hepatic Impairment

Memantine pharmacokinetics were evaluated following the administration of single oral doses of 20 mg in 8 subjects with moderate hepatic impairment (Child-Pugh Class B, score 7-9) and 8 subjects who were age-, gender-, and weight-matched to the hepatically-impaired subjects. There was no change in memantine exposure (based on Cmax and AUC) in subjects with moderate hepatic impairment as compared with healthy subjects. However, terminal elimination half-life increased by about 16% in subjects with moderate hepatic impairment as compared with healthy subjects.

Drug-Drug Interactions

Use with Cholinesterase Inhibitors

Coadministration of memantine with the AChE inhibitor donepezil HCl did not affect the pharmacokinetics of either compound. Furthermore, memantine did not affect AChE inhibition by donepezil. In a 24-week controlled clinical study in patients with moderate to severe Alzheimer's disease, the adverse reaction profile observed with a combination of memantine immediate-release and donepezil was similar to that of donepezil alone.

Effect of Memantine on the Metabolism of Other Drugs

In vitro studies conducted with marker substrates of CYP450 enzymes (CYP1A2, -2A6, -2C9, -2D6, -2E1, -3A4) showed minimal inhibition of these enzymes by memantine. In addition, in vitro studies indicate that at concentrations exceeding those associated with efficacy, memantine does not induce the cytochrome P450 isozymes CYP1A2, -2C9, -2E1 and -3A4/5. No pharmacokinetic interactions with drugs metabolized by these enzymes are expected.

Pharmacokinetic studies evaluated the potential of memantine for interaction with warfarin and bupropion. Memantine did not affect the pharmacokinetics of the CYP2B6 substrate bupropion or its metabolite hydroxybupropion. Furthermore, memantine did not affect the pharmacokinetics or pharmacodynamics of warfarin as assessed by the prothrombin INR.

Effect of Other Drugs on Memantine

Memantine is predominantly renally eliminated, and drugs that are substrates and/or inhibitors of the CYP450 system are not expected to alter the metabolism of memantine.

Drugs Eliminated via Renal Mechanisms

Because memantine is eliminated in part by tubular secretion, coadministration of drugs that use the same renal cationic system, including hydrochlorothiazide (HCTZ), triamterene (TA), metformin, cimetidine, ranitidine, quinidine, and nicotine, could potentially result in altered plasma levels of both agents. However, coadministration of memantine and HCTZ/TA did not affect the bioavailability of either memantine or TA, and the bioavailability of HCTZ decreased by 20%. In addition, coadministration of memantine with the antihyperglycemic drug Glucovance (glyburide and metformin HCl) did not affect the pharmacokinetics of memantine, metformin and glyburide. Furthermore, memantine did not modify the serum glucose lowering effect of Glucovance, indicating the absence of a pharmacodynamic interaction.

Drugs Highly Bound to Plasma Proteins

Because the plasma protein binding of memantine is low (45%), an interaction with drugs that are highly bound to plasma proteins, such as warfarin and digoxin, is unlikely.

13 NONCLINICAL TOXICOLOGY

13.1 Carcinogenesis, Mutagenesis, Impairment of Fertility

There was no evidence of carcinogenicity in a 113-week oral study in mice at doses up to 40 mg/kg/day (7 times the maximum recommended human dose [MRHD] on a mg/m^2 basis). There was also no evidence of carcinogenicity in rats orally dosed at up to 40 mg/kg/day for 71 weeks followed by 20 mg/kg/day (14 and 7 times the MRHD on a mg/m^2 basis, respectively) through 128 weeks.

Memantine produced no evidence of genotoxic potential when evaluated in the in vitro S. typhimurium or E. coli reverse mutation assay, an in vitro chromosomal aberration test in human lymphocytes, an in vivo cytogenetics assay for chromosome damage in rats, and the in vivo mouse micronucleus assay. The results were equivocal in an in vitro gene mutation assay using Chinese hamster V79 cells.

No impairment of fertility or reproductive performance was seen in rats administered up to 18 mg/kg/day (6 times the MRHD on a mg/m^2 basis) orally from 14 days prior to mating through gestation and lactation in females, or for 60 days prior to mating in males.

13.2 Animal Toxicology and /or Pharmacology

Memantine induced neuronal lesions (vacuolation and necrosis) in the multipolar and pyramidal cells in cortical layers III and IV of the posterior cingulate and retrosplenial neocortices in rats, similar to those which are known to occur in rodents administered other NMDA receptor antagonists. Lesions were seen after a single dose of memantine. In a study in which rats were given daily oral doses of memantine for 14 days, the no-effect dose for neuronal necrosis was 4 times the maximum recommended human dose (MRHD of 28 mg/day) on a mg/m^2 basis.

In acute and repeat-dose neurotoxicity studies in female rats, oral administration of memantine and donepezil in combination resulted in increased incidence, severity, and distribution of neurodegeneration compared with memantine alone. The no-effect levels of the combination were associated with clinically relevant plasma memantine and donepezil exposures.

The relevance of these findings to humans is unknown.

14 CLINICAL STUDIES

The effectiveness of NAMENDA XR as a treatment for patients with moderate to severe Alzheimer's disease was based on the results of a double-blind, placebo-controlled trial.

24-week Study of NAMENDA XR Capsules

This was a randomized double-blind clinical investigation in outpatients with moderate to severe Alzheimer's disease (diagnosed by DSM-IV criteria and NINCDS-ADRDA criteria for AD with a Mini Mental State Examination (MMSE) score ≥ 3 and ≤ 14 at Screening and Baseline) receiving acetylcholinesterase inhibitor (AChEI) therapy at a stable dose for 3 months prior to screening. The mean age of patients participating in this trial was 76.5 years with a range of 49-97 years. Approximately 72% of patients were female and 94% were Caucasian.

Study Outcome Measures

The effectiveness of NAMENDA XR was evaluated in this study using the co-primary efficacy parameters of Severe Impairment Battery (SIB) and the Clinician's Interview-Based Impression of Change (CIBIC-Plus).

The ability of NAMENDA XR to improve cognitive performance was assessed with the Severe Impairment Battery (SIB), a multi-item instrument that has been validated for the evaluation of cognitive function in patients with moderate to severe dementia. The SIB examines selected aspects of cognitive performance, including elements of attention, orientation, language, memory, visuospatial ability, construction, praxis, and social interaction. The SIB scoring range is from 0 to 100, with lower scores indicating greater cognitive impairment.

The ability of NAMENDA XR to produce an overall clinical effect was assessed using a Clinician's Interview Based Impression of Change that required the use of caregiver information, the CIBIC-Plus. The CIBIC-Plus is not a single instrument and is not a standardized instrument like the ADCS-ADL or SIB. Clinical trials for investigational drugs have used a variety of CIBIC formats, each different in terms of depth and structure. As such, results from a CIBIC-Plus reflect clinical experience from the trial or trials in which it was used and cannot be compared directly with the results of CIBIC-Plus evaluations from other clinical trials. The CIBIC-Plus used in this trial was a structured instrument based on a comprehensive evaluation at baseline and subsequent time-points of four domains: general (overall clinical status), functional (including activities of daily living), cognitive, and behavioral. It represents the assessment of a skilled clinician using validated scales based on his/her observation during an interview with the patient, in combination with information supplied by a caregiver familiar with the behavior of the patient over the interval rated. The CIBIC-Plus is scored as a seven point categorical rating, ranging from a score of 1, indicating “marked improvement” to a score of 4, indicating “no change” to a score of 7, indicating “marked worsening.” The CIBIC-Plus has not been systematically compared directly to assessments not using information from caregivers (CIBIC) or other global methods.

Study Results

In this study, 677 patients were randomized to one of the following 2 treatments: NAMENDA XR 28 mg/day or placebo while still receiving an AChEI (either donepezil, galantamine, or rivastigmine).

Effects on Severe Impairment Battery (SIB)

Figure 1 shows the time course for the change from baseline in SIB score for the two treatment groups completing the 24 weeks of the study. At 24 weeks of treatment, the mean difference in the SIB change scores for the NAMENDA XR 28 mg/AChEI-treated (combination therapy) patients compared to the patients on placebo/AChEI (monotherapy) was 2.6 units. Using an LOCF analysis, NAMENDA XR 28 mg/AChEI treatment was statistically significantly superior to placebo/AChEI.

Figure 1: Time course of the change from baseline in SIB score for patients completing 24 weeks of treatment.

Figure 2 shows the cumulative percentages of patients from each treatment group who had attained at least the measure of improvement in SIB score shown on the X axis. The curves show that both patients assigned to NAMENDA XR 28 mg/AChEI and placebo/AChEI have a wide range of responses, but that the NAMENDA XR 28 mg/AChEI group is more likely to show an improvement or a smaller decline.

Figure 2: Cumulative percentage of patients completing 24 weeks of double-blind treatment with specified changes from baseline in SIB scores.

Figure 3 shows the time course for the CIBIC-Plus score for patients in the two treatment groups completing the 24 weeks of the study. At 24 weeks of treatment, the mean difference in the CIBIC-Plus scores for the NAMENDA XR 28 mg/AChEI-treated patients compared to the patients on placebo/AChEI was 0.3 units. Using an LOCF analysis, NAMENDA XR 28 mg/AChEI treatment was statistically significantly superior to placebo/AChEI.

Figure 3: Time course of the CIBIC-Plus score for patients completing 24 weeks of treatment.

Figure 4 is a histogram of the percentage distribution of CIBIC-Plus scores attained by patients assigned to each of the treatment groups who completed 24 weeks of treatment.

Figure 4: Distribution of CIBIC-Plus ratings at week 24.

16 HOW SUPPLIED/STORAGE AND HANDLING

Product: 68151-5755

NDC: 68151-5755-8 1 CAPSULE, EXTENDED RELEASE in a CUP

Product: 68151-5829

NDC: 68151-5829-8 1 CAPSULE, EXTENDED RELEASE in a BOTTLE

17 PATIENT COUNSELING INFORMATION

Advise the patient to read the FDA-approved patient labeling (Patient Information).

- To assure safe and effective use of NAMENDA XR, the information and instructions provided in the patient information section should be discussed with patients and caregivers.
- Instruct patients and caregivers to take NAMENDA XR only once per day, as prescribed.
- Instruct patients and caregivers that NAMENDA XR capsules be swallowed whole. Alternatively, NAMENDA XR capsules may be opened and sprinkled on applesauce and the entire contents should be consumed. The capsules should not be divided, chewed or crushed.
- Warn patients not to use any capsules of NAMENDA XR that are damaged or show signs of tampering.
- If a patient misses a single dose of NAMENDA XR, that patient should not double up on the next dose. The next dose should be taken as scheduled. If a patient fails to take NAMENDA XR for several days, dosing should not be resumed without consulting that patient's healthcare professional.
- Advise patients and caregivers that NAMENDA XR may cause headache, diarrhea, and dizziness.

Distributed by:
Allergan USA, Inc.
Irvine, CA 92612

Manufactured by:
Forest Laboratories Ireland Ltd

Licensed from Merz Pharmaceuticals GmbH

© 2017 Allergan. All rights reserved

Patient Information

NAMENDA XR [Nuh-MEN-dah Eks-Are]
(memantine hydrochloride) Extended-Release Capsules

Read this Patient Information that comes with NAMENDA XR before you start taking it and each time you get a refill. There may be new information. This information does not take the place of talking to your doctor about your medical condition or your treatment.

What is NAMENDA XR?

NAMENDA XR is a prescription medicine used for the treatment of moderate to severe dementia in people with Alzheimer's disease. NAMENDA XR belongs to a class of medicines called NMDA (N-methyl-D-aspartate) inhibitors.

It is not known if NAMENDA XR is safe and effective in children.

Who should not take NAMENDA XR?

Do not take NAMENDA XR if you are allergic to memantine or any of the other ingredients in NAMENDA XR. See the end of this leaflet for a complete list of ingredients in NAMENDA XR.

What should I tell my doctor before taking NAMENDA XR?

Before you take NAMENDA XR, tell your doctor if you:

- have or have had seizures
- have or have had problems passing urine
- have or have had bladder or kidney problems
- have liver problems
- have any other medical conditions
- are pregnant or plan to become pregnant. It is not known if NAMENDA XR will harm your unborn baby.
- are breastfeeding or plan to breastfeed. It is not known if NAMENDA XR passes into your breast milk. You and your doctor should decide if you will take NAMENDA XR or breastfeed.

Tell your doctor about all the medicines you take, including prescription and non-prescription medicines, vitamins, and herbal supplements.

Taking NAMENDA XR with certain other medicines may affect each other. Taking NAMENDA XR with other medicines can cause serious side effects.

Especially tell your doctor if you take:

- other NMDA antagonists such as amantadine, ketamine, and dextromethorphan
- medicines that make your urine alkaline such as carbonic anhydrase inhibitors and sodium bicarbonate

Ask your doctor or pharmacist for a list of these medicines, if you are not sure.

Know the medicines you take. Keep a list of them to show your doctor and pharmacist when you get a new medicine.

How should I take NAMENDA XR?

- Your doctor will tell you how much NAMENDA XR to take and when to take it.
- Your doctor may change your dose if needed.
- NAMENDA XR may be taken with food or without food.
- NAMENDA XR capsules may be opened and sprinkled on applesauce before swallowing, but the contents of the entire capsule should be taken and the dose should not be divided. Except when opened and sprinkled on applesauce, NAMENDA XR capsules must be swallowed whole and never crushed, divided or chewed.

Do not use any capsules of NAMENDA XR that are damaged or show signs of tampering.

- If you are currently taking another formulation of memantine, talk to your healthcare professional about how to switch to NAMENDA XR.
- If you forget to take one dose of NAMENDA XR, do not double up on the next dose. You should take only the next dose as scheduled.
- If you have forgotten to take NAMENDA XR for several days, you should not take the next dose until you talk to your doctor.
- If you take too much NAMENDA XR, call your doctor or poison control center at 1-800-222-1222 right away, or go to the nearest hospital emergency room.

What are the possible side effects of NAMENDA XR?

NAMENDA XR may cause side effects, including:

The most common side effects of NAMENDA XR include:

- headache
- diarrhea
- dizziness

These are not all the possible side effects of NAMENDA XR. For more information, ask your doctor or pharmacist.

Call your doctor for medical advice about side effects. You may report side effects to FDA at 1-800-FDA-1088.

How should I store NAMENDA XR?

- Store NAMENDA XR at room temperature between 68°F to 77°F (20°C to 25°C).

What are the ingredients in NAMENDA XR?

Active ingredient: memantine hydrochloride

Inactive ingredients: sugar spheres, polyvinylpyrrolidone, hypromellose, talc, polyethylene glycol, ethylcellulose, ammonium hydroxide, oleic acid, and medium chain triglycerides

Keep NAMENDA XR and all medicines out of the reach of children.

General information about the safe and effective use of NAMENDA XR:

Medicines are sometimes prescribed for purposes other than those listed in a Patient Information leaflet. Do not take NAMENDA XR for a condition for which it was not prescribed. Do not give NAMENDA XR to other people, even if they have the same condition. It may harm them.

This Patient Information leaflet summarizes the most important information about NAMENDA XR. If you would like more information, talk with your doctor. You can ask your doctor or pharmacist for information about NAMENDA XR that was written for healthcare professionals.

For more information about NAMENDA XR, go to www.namendaxr.com, or call Allergan at 1-800-678-1605.

This Patient Information has been approved by the U.S. Food and Drug Administration.

Distributed by:
Allergan USA, Inc.
Irvine, CA 92612

Manufactured by:
Forest Laboratories Ireland Ltd

Licensed from Merz Pharmaceuticals GmbH

Revised: 10/2016

© 2017 Allergan. All rights reserved

NAMENDA XR® is a registered trademark of Merz Pharma GmbH & Co. KGaA